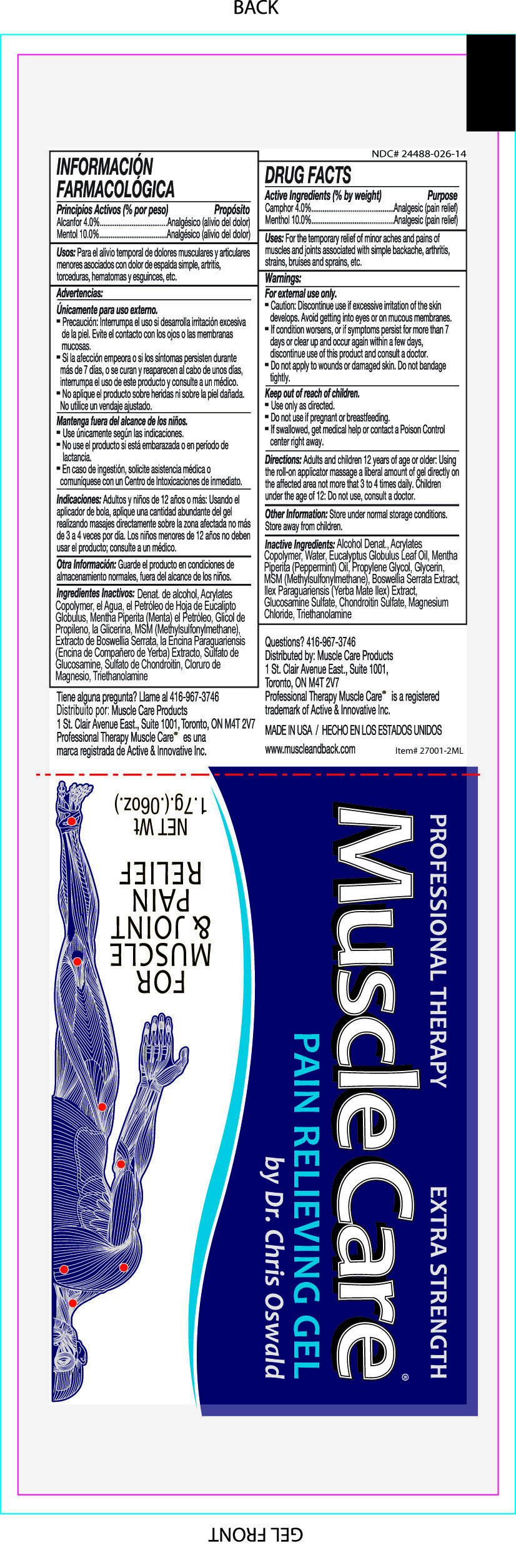 DRUG LABEL: MuscleCare
NDC: 24488-026 | Form: GEL
Manufacturer: Active and Innovative
Category: otc | Type: HUMAN OTC DRUG LABEL
Date: 20110623

ACTIVE INGREDIENTS: MENTHOL .17 g/1.7 g; CAMPHOR (SYNTHETIC) .068 g/1.7 g
INACTIVE INGREDIENTS: ALCOHOL; POLYACRYLIC ACID (800000 MW); WATER; EUCALYPTUS OIL; PEPPERMINT OIL; PROPYLENE GLYCOL; GLYCERIN; DIMETHYL SULFONE; INDIAN FRANKINCENSE; ILEX PARAGUARIENSIS LEAF; GLUCOSAMINE SULFATE; SULFATE ION; MAGNESIUM CHLORIDE; TROLAMINE

Drug Facts:

Active Ingredients

Camphor 4.0%

Menthol 10.0%

Purpose

Analgesic (Pain Relief)

Analgesic (Pain Relief)

Uses:

For the temporary relief of minor aches and pains of muscles and joints associated with simple backache, arthritis, strains, bruises and sprains, etc.

Warnings:

For external use only.

- Caution: Discontinue use if excessive irritation of the skin develops. Avoid getting into eyes or on mucous membranes.
- If condition worsens, or if symptoms persist for more than 7 days or clear up and occur again with in a few days, discontinue use of this products and consult a doctor.
- Do not apply to wounds or damaged skin. Do not bandage tightly.

Keep out of reach of children

- Use only as directed.
- Do not use if pregnant or breastfeeding.
- If swallowed, get medical help or contact a Poison Control center right away.

Directions:

Adults and children 12 years of age or older. Using the roll-on applicator, message a liberal amount of gel directly on the affected area not more than 3 to 4 daily. Children under the age of 12: Do not use, consult a doctor.

STORAGE AND HANDLING

Store under normal storage conditions. Store away from children.

Inactive Ingredients

Alcohol Denat, Acrylates Copolymer, Water, Eucalyptus Globulus Leaf Oil, Mentha Piperita (Peppermint) Oil, Propylene Glycol, Glycerin, MSM (Methylsulfonymethane), Boswellia Serrata Extract, Glucosamine Sulfate, Chondroitin Sulfate, Magnesium Chloride, Triethanolamine

Questions?

416-967-3746

PACKAGE LABEL

Placeholder Text